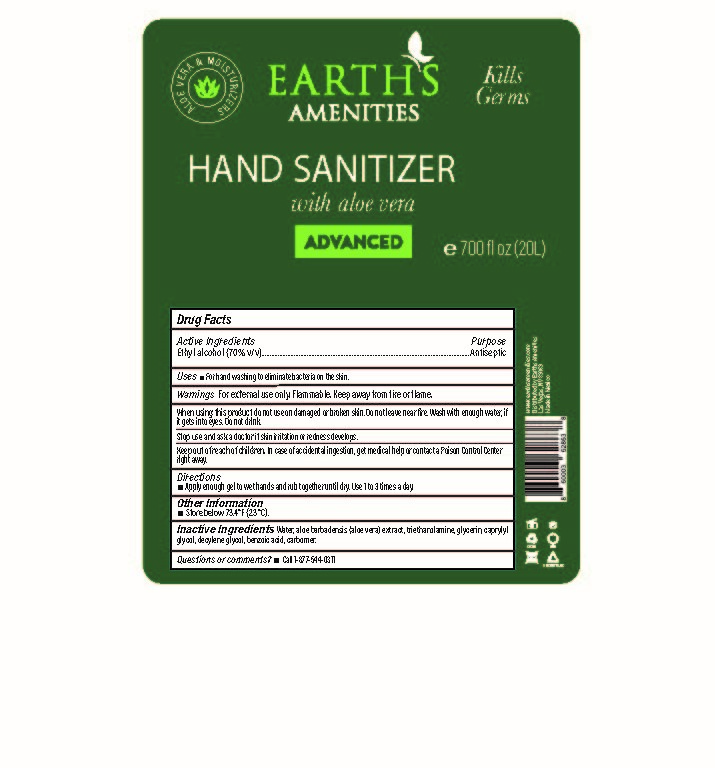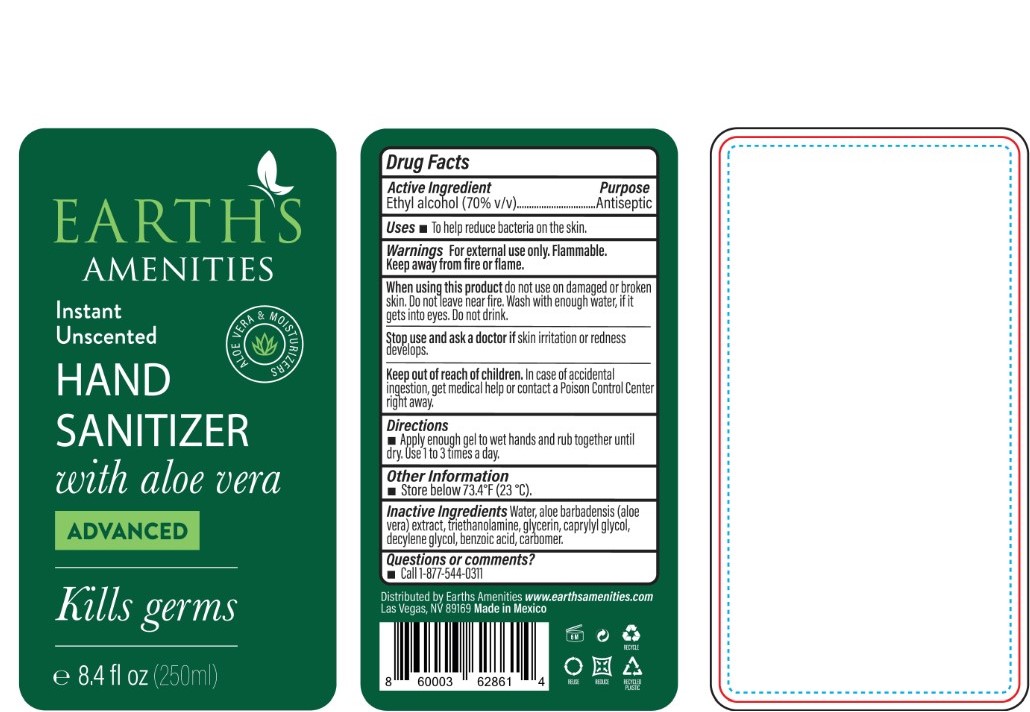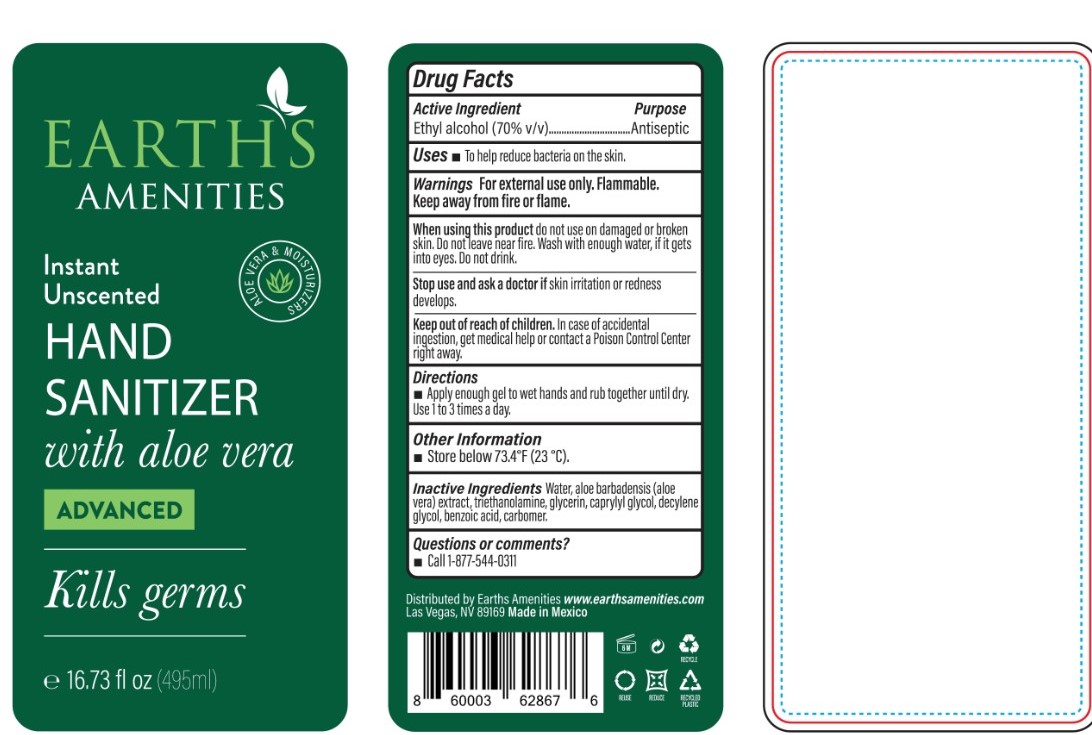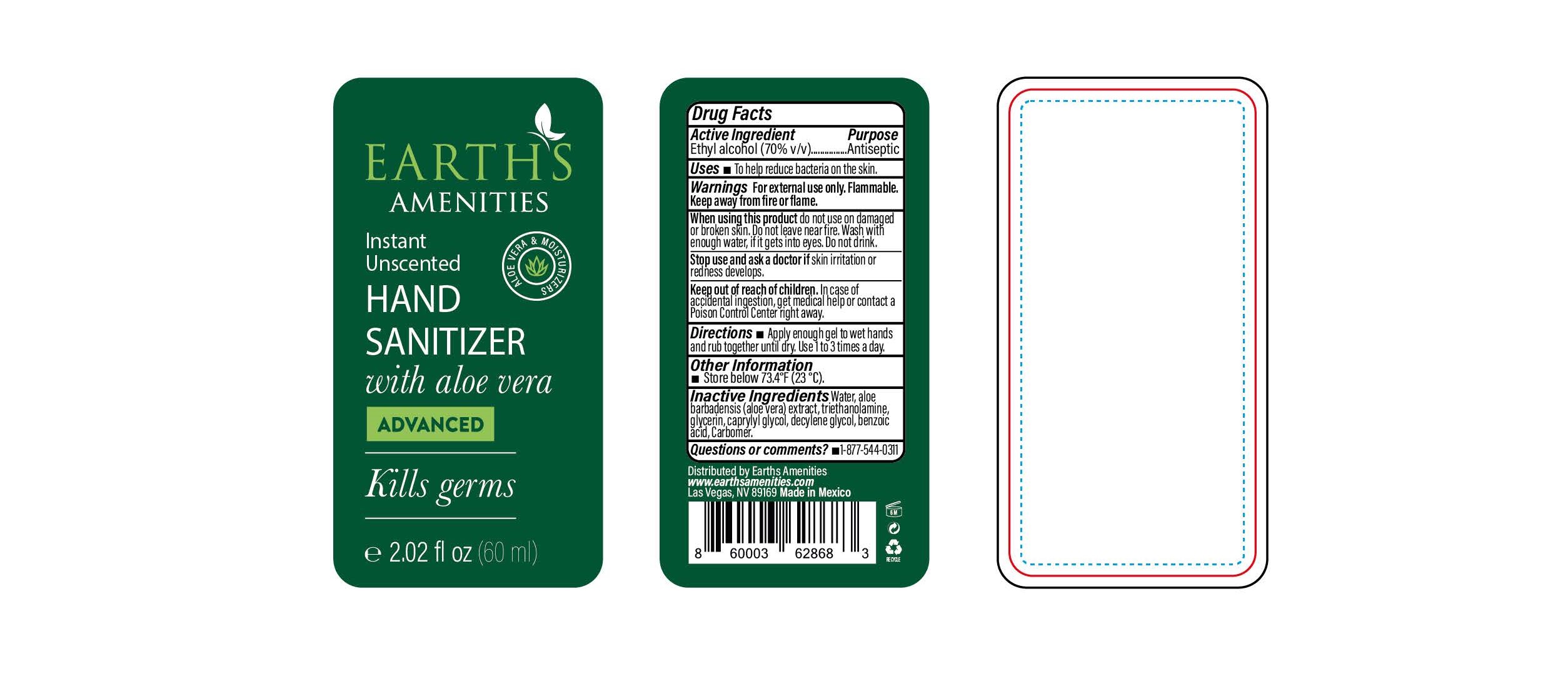 DRUG LABEL: Instant Unscented Hand Sanitizer with aloe vera Advanced
NDC: 74949-002 | Form: LIQUID
Manufacturer: Earths Amenities
Category: otc | Type: HUMAN OTC DRUG LABEL
Date: 20200428

ACTIVE INGREDIENTS: ALCOHOL 70 mL/100 mL
INACTIVE INGREDIENTS: TROLAMINE 0.9 mL/100 mL; GLYCERIN 0.1 mL/100 mL; ALOE VERA FLOWER 5 mL/100 mL; WATER 25 mL/100 mL; BENZOIC ACID 0.1 mL/100 mL; CARBOMER 940 0.5 mL/100 mL; CAPRYLYL GLYCOL 0.1 mL/100 mL; DECYLENE GLYCOL 0.1 mL/100 mL

The hand sanitizer is manufactured using only the following United States Pharmacopoeia (USP) grade ingredients in the preparation of the product (percentage in final product formulation) :

1. Alcohol (ethanol) (USP or Food Chemical Codex (FCC) grade) (70%, volume/volume (v/v)) in an aqueous solution denatured according to Alcohol and Tobacco Tax and Trade Bureau regulations in 27 CFR part 20.
2. Glycerin
3. Aloe Vera Extract
4. Water
5. Caprylyl Glycol
6. Decylene Glycol
7. Benzoic Acid
8. Carbomer
9. Triethanolamine

The firm does not add other active or inactive ingredients. Different or additional ingredients may impact the quality and potency of the product.

Active Ingredient(s)

Ethyl Alcohol 70% v/v. Purpose: Antiseptic

Uses

Antiseptic

Warnings

For external use only. Flammable. Keep away from fire or flame

When using this product do not use on damaged or broken skin. Do not leave near fire. Wash with enough water, if it gets into eyes. Do not drink

Stop use and ask a doctor if skin irritation or redness develops.

Keep out of reach of children. In case of accidental ingestion, get medical help or contact a Poison Control Center right away.

Directions

Apply enough gel to wet hands and rub together until dry. Use 1 to 3 times a day.

Other information

Store below 73.4F (23C)

Inactive ingredients

Water, aloe barbadensis (aloe vera extract), triethanolamine, glycerin, caprylyl glycol, decylene glycol, benzoic acid, carbomer

INDICATIONS AND USAGE

To help reduce bacteria on the skin

Package Label - Principal Display Panel

60 mL NDC: 74949-002-60

250 mL NDC: 74949-002-25

495 mL NDC: 74949-002-49

20000 mL NDC: 74949-002-20